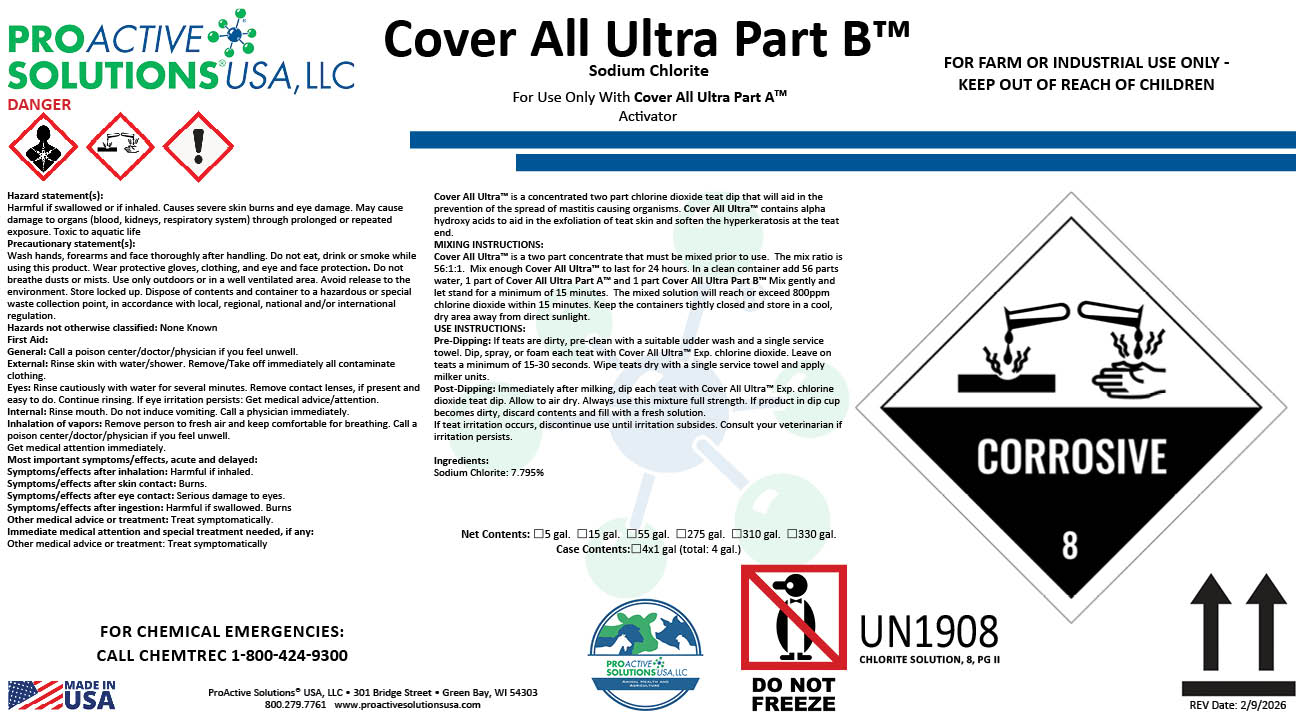 DRUG LABEL: Cover All Ultra Part B
NDC: 63927-4124 | Form: SOLUTION
Manufacturer: ProActive Solutions USA, LLC
Category: animal | Type: OTC ANIMAL DRUG LABEL
Date: 20260210

ACTIVE INGREDIENTS: SODIUM CHLORITE 7.795 kg/100 kg

Cover All Ultra Part B

DESCRIPTION

Cover All Ultra™ is a concentrated two part chlorine dioxide teat dip that will aid in the
prevention of the spread of mastitis causing organisms. Cover All Ultra™ contains alpha
hydroxy acids to aid in the exfoliation of teat skin and soften the hyperkeratosis at the teat
end.
MIXING INSTRUCTIONS:
Cover All Ultra™ is a two part concentrate that must be mixed prior to use. The mix ratio is
56:1:1. Mix enough Cover All Ultra™ to last for 24 hours. In a clean container add 56 parts
water, 1 part of Cover All Ultra Part A™ and 1 part Cover All Ultra Part B™ Mix gently and
let stand for a minimum of 15 minutes. The mixed solution will reach or exceed 800ppm
chlorine dioxide within 15 minutes. Keep the containers tightly closed and store in a cool,
dry area away from direct sunlight.
USE INSTRUCTIONS:
Pre-Dipping: If teats are dirty, pre-clean with a suitable udder wash and a single service
towel. Dip, spray, or foam each teat with Cover All Ultra™ Exp. chlorine dioxide. Leave on
teats a minimum of 15-30 seconds. Wipe teats dry with a single service towel and apply
milker units.
Post-Dipping: Immediately after milking, dip each teat with Cover All Ultra™ Exp. chlorine
dioxide teat dip. Allow to air dry. Always use this mixture full strength. If product in dip cup
becomes dirty, discard contents and fill with a fresh solution.
If teat irritation occurs, discontinue use until irritation subsides. Consult your veterinarian if
irritation persists.
Ingredients:
Sodium Chlorite: 7.795%

Hazard statement(s):
Harmful if swallowed or if inhaled. Causes severe skin burns and eye damage. May cause
damage to organs (blood, kidneys, respiratory system) through prolonged or repeated
exposure. Toxic to aquatic life
Precautionary statement(s):
Wash hands, forearms and face thoroughly after handling. Do not eat, drink or smoke while
using this product. Wear protective gloves, clothing, and eye and face protection. Do not
breathe dusts or mists. Use only outdoors or in a well ventilated area. Avoid release to the
environment. Store locked up. Dispose of contents and container to a hazardous or special
waste collection point, in accordance with local, regional, national and/or international
regulation.
Hazards not otherwise classified: None Known
First Aid:
General: Call a poison center/doctor/physician if you feel unwell.
External: Rinse skin with water/shower. Remove/Take off immediately all contaminate
clothing.
Eyes: Rinse cautiously with water for several minutes. Remove contact lenses, if present and
easy to do. Continue rinsing. If eye irritation persists: Get medical advice/attention.
Internal: Rinse mouth. Do not induce vomiting. Call a physician immediately.
Inhalation of vapors: Remove person to fresh air and keep comfortable for breathing. Call a
poison center/doctor/physician if you feel unwell.
Get medical attention immediately.
Most important symptoms/effects, acute and delayed:
Symptoms/effects after inhalation: Harmful if inhaled.
Symptoms/effects after skin contact: Burns.
Symptoms/effects after eye contact: Serious damage to eyes.
Symptoms/effects after ingestion: Harmful if swallowed. Burns
Other medical advice or treatment: Treat symptomatically.
Immediate medical attention and special treatment needed, if any:
Other medical advice or treatment: Treat symptomatically